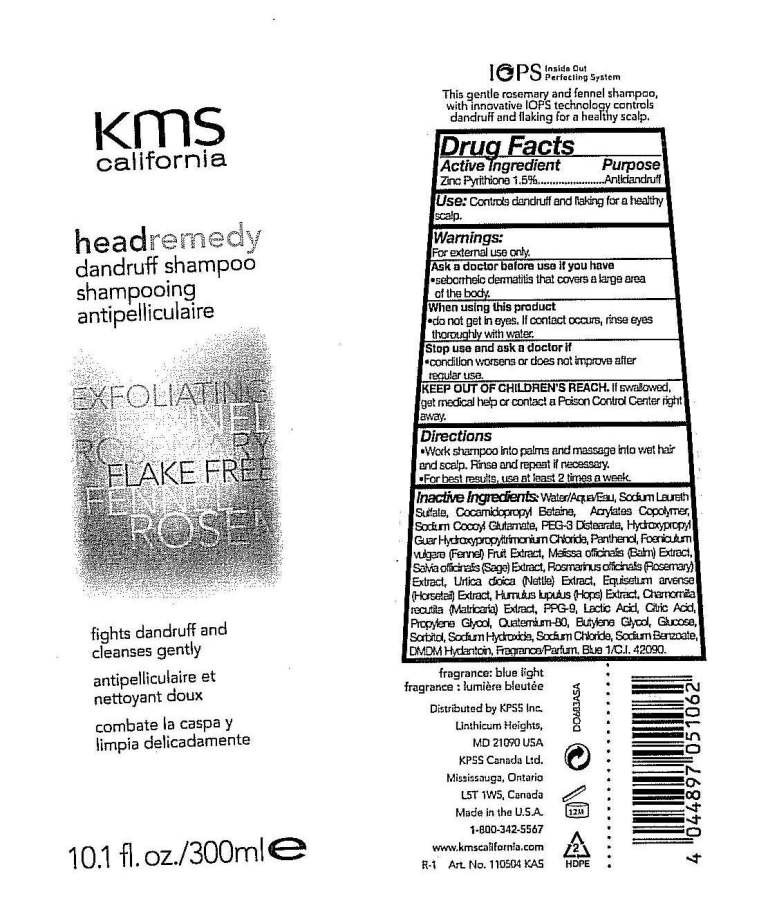 DRUG LABEL: Head Remedy
NDC: 25237-0515 | Form: SHAMPOO
Manufacturer: KPSS Inc.
Category: otc | Type: HUMAN OTC DRUG LABEL
Date: 20100819

ACTIVE INGREDIENTS: Pyrithione Zinc 1.5 g/100 g

Drug Facts

Active Ingredient: Zinc Pyrithione 1.5%

Purpose: Antidandruff

INDICATIONS AND USAGE

Use: Controls dandruff and flaking for a healthy scalp.

Warnings: For external use only.

Ask a doctor before use if you have: seborrheic dermatitis that covers a large area of the body.

When using this product: do not get in eyes. If contact occurs, rinse eyes thoroughly with water.

Stop use and ask a doctor if: condition worsens or does not improve after regular use.

KEEP OUT OF REACH OF CHILDREN

Keep out of children's reach. If swallowed, get medical help or contact a Poison Control Center right away.

DOSAGE AND ADMINISTRATION

Directions: Work shampoo into palms and massage into wet hair and scalp. Rinse and repeat if necessary. For best results, use at least 2 times a week.

QUESTIONS

Distributed by KPSS Inc., Lithicum Heights, MD 21090 USA, 1-800-342-5567

PACKAGE LABEL

MM1 : 10oz_dandruff_shampoo_label.jpg

INACTIVE INGREDIENT

water, sodium laureth sulfate, cocamidopropyl betaine, acrylates copolymer, sodium cocyl glutamate, PEG-3 distearate, hydroxypropyl guar hydroxypropyltrimonium chloride, panthenol, Foeniculum vulgare (Fennel) fruit extract, Malissa officinalis (Balm) extract, Salvia officinalis (Sage) extract, Rosmarinus officinalis (Rosemary) extract, Urtica dioica (Nettle) extract, Equisetum arvense (Horsetail) extract, Humulus lupulus (Hops) extract, Chamomilla recutita (Matricaria) extract, PPG-9, lactic acid, citric acid, propylene glycol, quaternium-80, butylene glycol, glucose, sorbitol, sodium hydroxide, sodium chloride, sodium benzoate, DMDM Hydantoin, fragrance, Blue 1